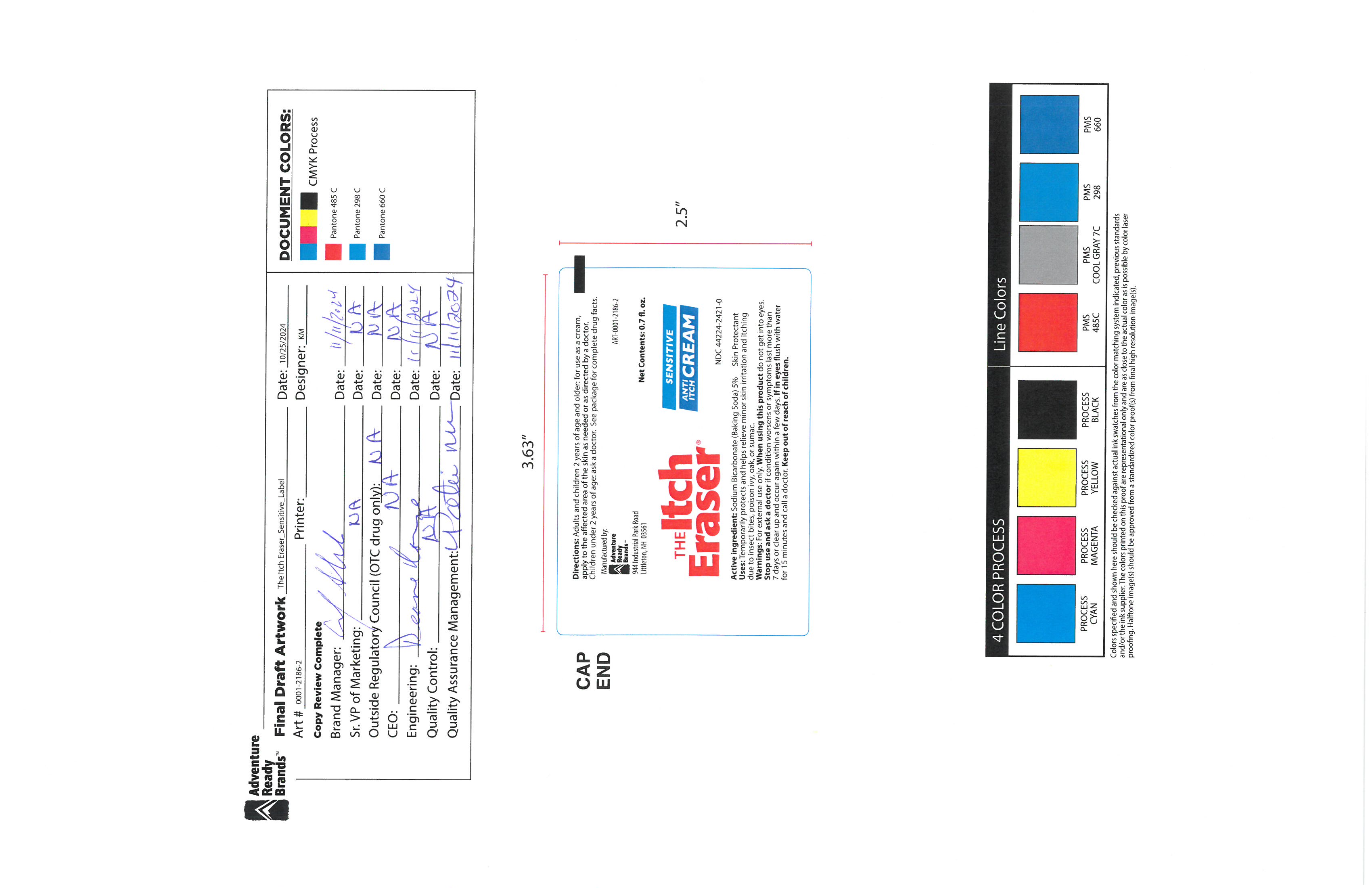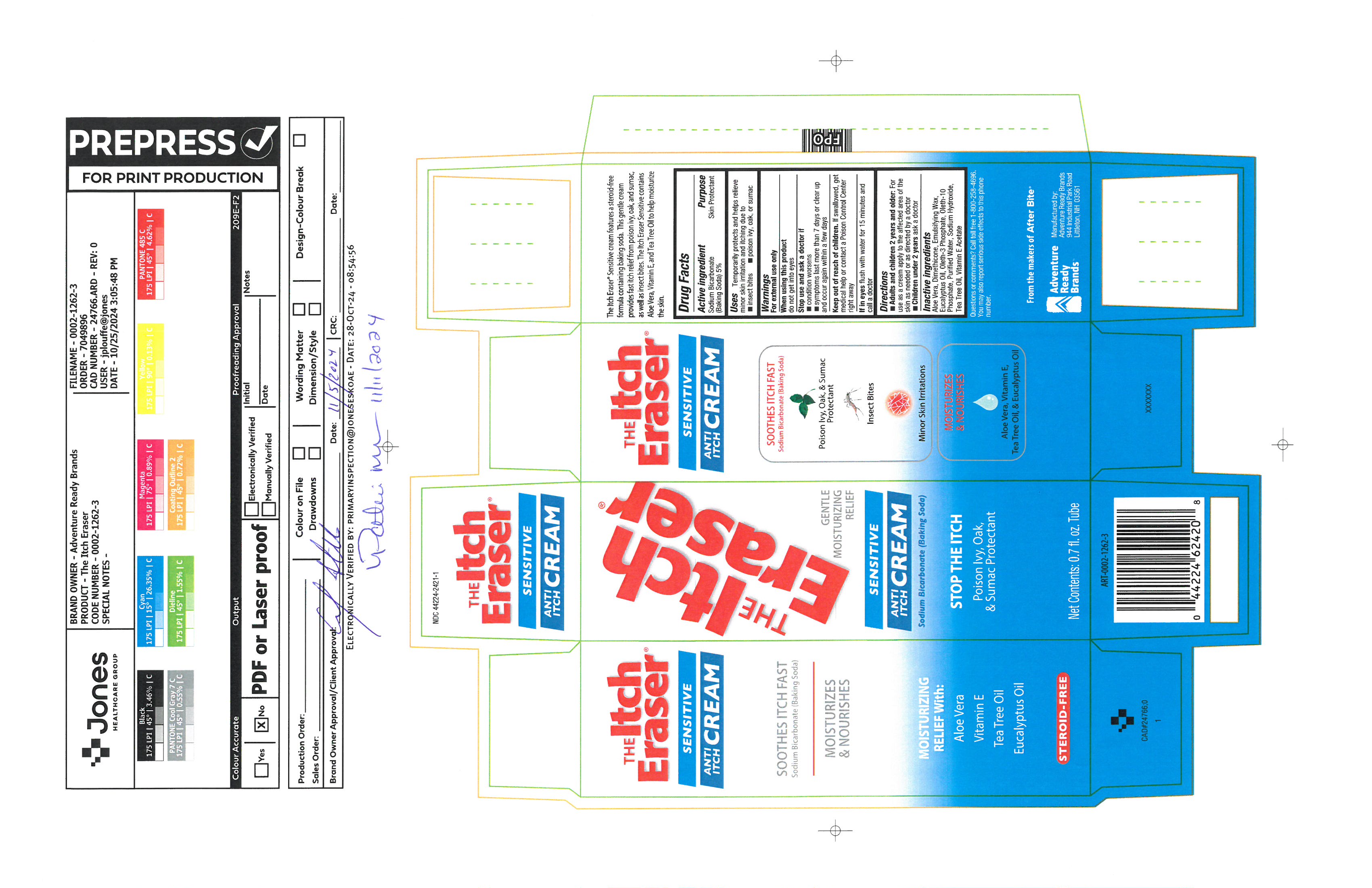 DRUG LABEL: Itch Eraser Sensitive
NDC: 44224-2421 | Form: CREAM
Manufacturer: Tender Corporation d/b/a Adventure Ready Brands
Category: otc | Type: HUMAN OTC DRUG LABEL
Date: 20251118

ACTIVE INGREDIENTS: SODIUM BICARBONATE 1.04 g/20 g
INACTIVE INGREDIENTS: .ALPHA.-TOCOPHEROL 0.1 g/20 g; DIMETHICONE 350 0.1 g/20 g; EUCALYPTUS OIL 0.26 g/20 g; ALOE VERA LEAF 1.1 g/20 g; TEA TREE OIL 0.2 g/20 g; OLETH-10 0.28 g/20 g; OLETH-3 PHOSPHATE 0.5 g/20 g; WHITE WAX 2 g/20 g; SODIUM HYDROXIDE 0.33 g/20 g; WATER 14.1 g/20 g

Itch Eraser Sensitive

Active Ingredient

Sodium Bicarbonate

(Baaking Soda) 5%

Purpose

Sin Protectant

Uses

Temporarily protects and helps relieve minor skin irritation and itchng due to insect bites, poison ivy, oak, or sumac

Warnings

For external use only

When using this product

do not get into eyes

Stop use and Ask a doctor if

condition worsens, symptoms last more than 7 days or clear up and occur again within a few days

Keep out of reach of children

If Swallowed, get medical help or contact posion control center right away.

If in eyes

flush with watere for 15 minutes and call a doctor

Directions

Adults and children 2 yearss and older. For use as a cream apply to the affeted area of the skin as needed or as direcred by a doctor. Children under 2 years ask a doctor

Inactive ingredients

aloe vera, dimethicone, emulsifying wax, eucalyptus oil, oleth-3 phosphate, oleth-10 phosphate, purified water, sodium hydroxde, tea tree oil, vitamine e acetate.